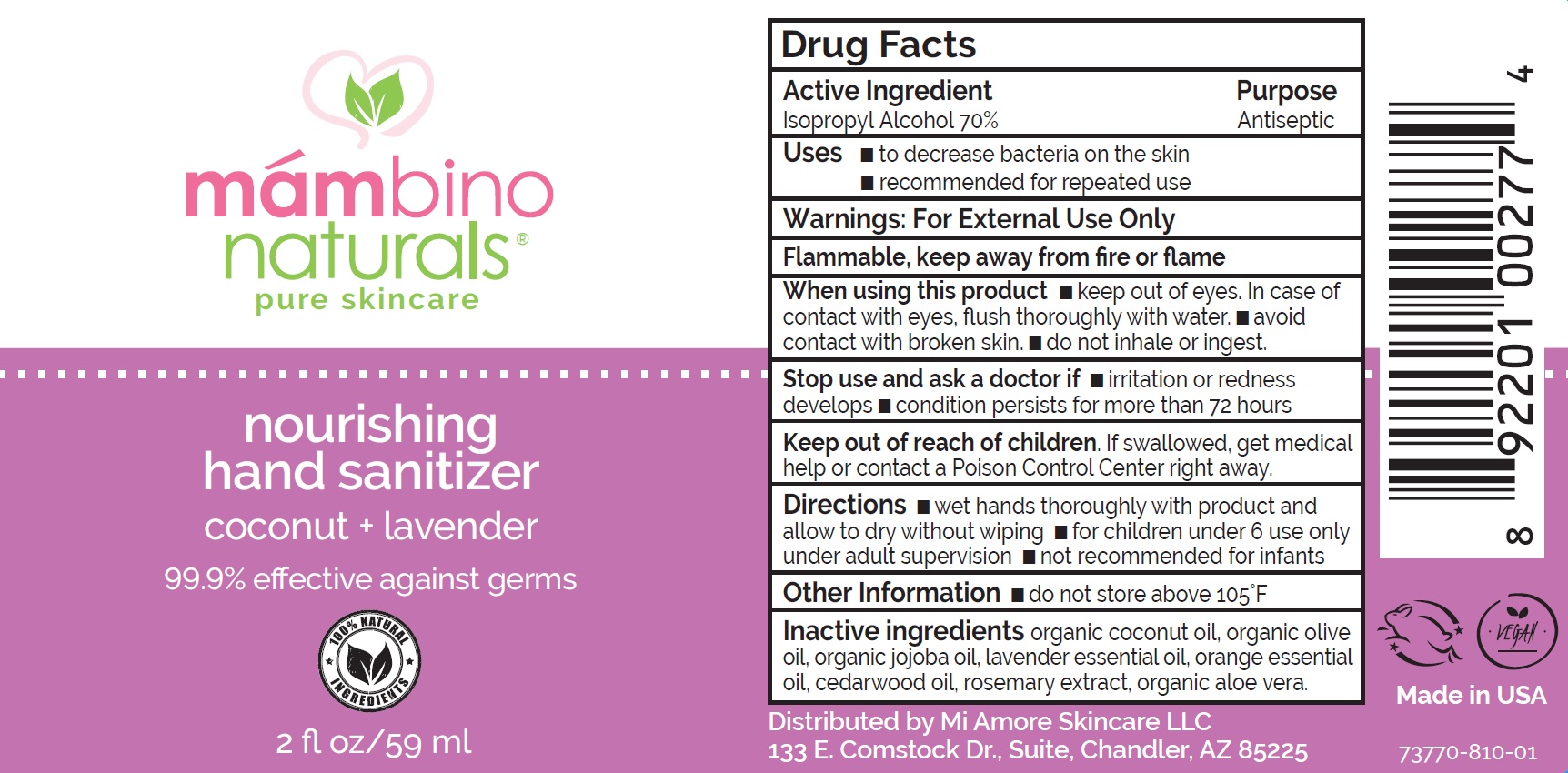 DRUG LABEL: Hand Sanitizer
NDC: 73770-810 | Form: SPRAY
Manufacturer: Mi Amore Skincare, LLC
Category: otc | Type: HUMAN OTC DRUG LABEL
Date: 20241213

ACTIVE INGREDIENTS: ISOPROPYL ALCOHOL 41.3 mL/59 mL
INACTIVE INGREDIENTS: JOJOBA OIL 2 mL/59 mL; COCONUT OIL 2 mL/59 mL; OLIVE OIL 2 mL/59 mL; BITTER ORANGE OIL 0.6 mL/59 mL; CEDAR LEAF OIL 0.6 mL/59 mL; SUNFLOWER OIL MONOGLYCERIDES 2 mL/59 mL; ALOE VERA LEAF 3 mL/59 mL; SHEA BUTTER 2 mL/59 mL; GLYCERIN 2 mL/59 mL; LAVENDER OIL 1 mL/59 mL; ROSEMARY OIL 0.5 mL/59 mL

DOSAGE AND ADMINISTRATION

- wet hands thoroughly with product and allow to dry without wiping
- for children under 6 use only under adult supervision
- not recommended for infants

WARNINGS

For External Use Only

Flammable, keep away from fire or flame

INACTIVE INGREDIENT

organic coconut oil, organic olive oil, organic jojoba oil, lavender essential oil, orange essential oil, cedarwood oil, rosemary extract, organic aloe vera.

INDICATIONS AND USAGE

- to decrease bacteria on the skin
- recommended for repeated use

KEEP OUT OF REACH OF CHILDREN

If swallowed, get medical help or contact a Poison Control Center right away.

PURPOSE

Antiseptic, Hand Sanitizer

ACTIVE INGREDIENT

Isopropyl Alcohol 70% v/v. Purpose: Antiseptic